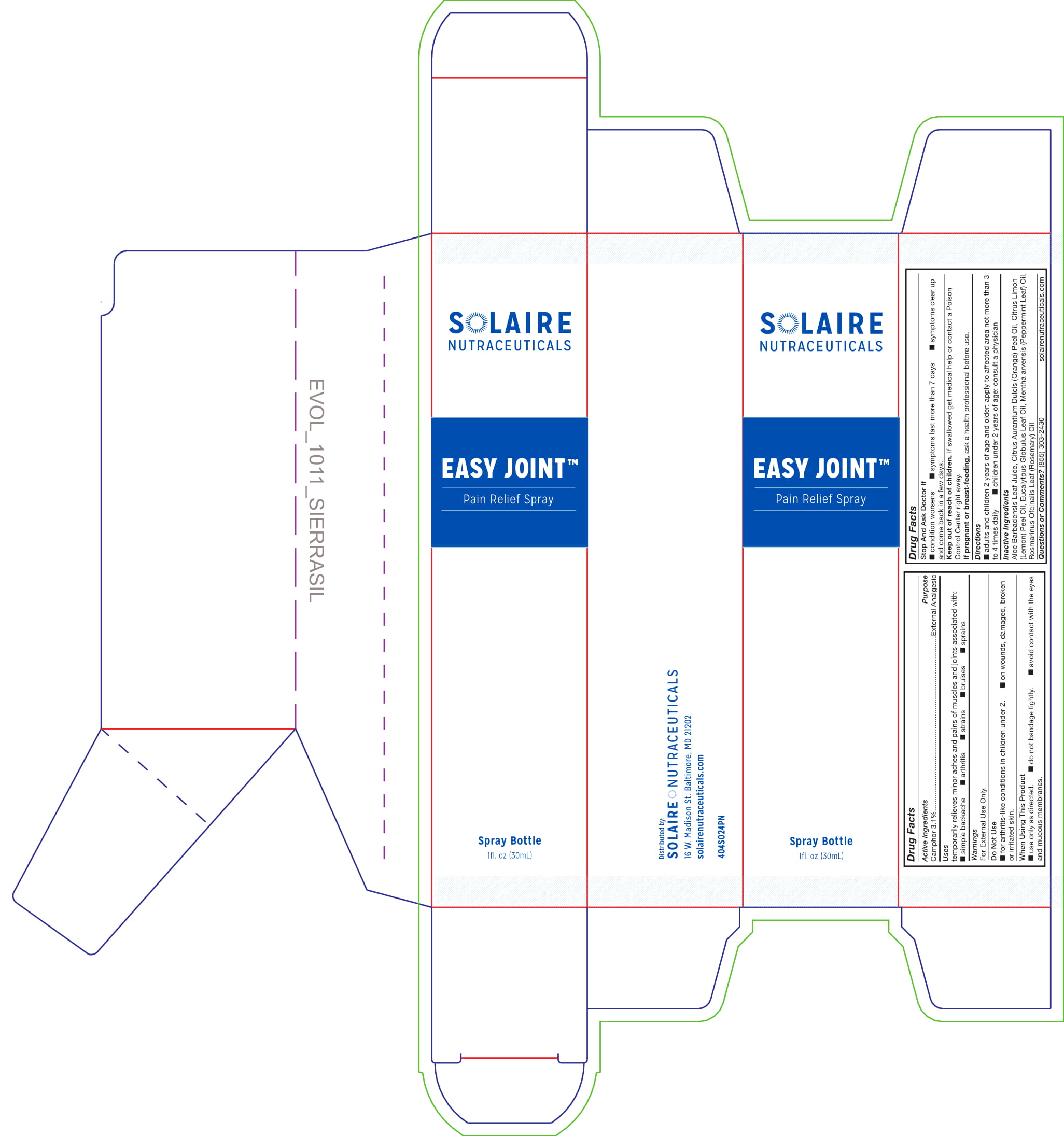 DRUG LABEL: Easy Joint
NDC: 72608-003 | Form: SPRAY
Manufacturer: D&d Essential Oils, Llc.,
Category: otc | Type: HUMAN OTC DRUG LABEL
Date: 20181014

ACTIVE INGREDIENTS: CAMPHOR (NATURAL) 3.1 g/100 mL
INACTIVE INGREDIENTS: ALOE VERA LEAF; ORANGE OIL; LEMON OIL; EUCALYPTUS OIL; MENTHA ARVENSIS FLOWER OIL; ROSEMARY OIL

ACTIVE INGREDIENT

Camphor 3.1%

PURPOSE

Camphor 3.1%.........................................Topical analgesic

INDICATIONS AND USAGE

temporarily relieves minor aches and pains of muscles and joints associated with:

- simple backache
- arthritis
- strains
- bruises
- sprains

WARNINGS

For external use only.

Do Not Use

- for arthritis-like conditions in children under 2.
- on wounds, damaged, broken or irritated skin

When Using This Product

- use only as directed.
- do not bandage tightly.
- avoid contact with eyes or mucous membranes.

Stop And Ask Doctor If

- condition worsens
- symptoms last more than 7 days
- symptoms clear up and com back in a few days

Keep out of reach of children. If swalled get medical help or contact a Poison Control Center right away.

PREGNANCY OR BREAST FEEDING

If pregnant or breast-feeding, ask a health professional before use.

DOSAGE AND ADMINISTRATION

- adults and children 2 yrs of age and older: apply to affected area not more than 3 to 4 times daily
- children under 2 yrs of age: consult a physician

INACTIVE INGREDIENT

Aloe Barbadensis Leaf Juice, Citrus Aurantium Dulcis (Orange) Peel Oil, Citrus Limon (Lemon) Peel Oil, Eucalyptus Globulus Leaf Oil, Mentha arvensis (Peppermint) Oil, Rosmarinus Officinalis Leaf (Rosemary) Oil

QUESTIONS

(855) 303-2430

solairenutraceuticals.com

DESCRIPTION

Distributed by Solaire Nutraceuticals

16 W. Madison St. Baltimore, MD 21202

solairenutraceuticals.com

4O4SO24PN

PACKAGE LABEL

SOLAIRE

NUTRACEUTICALS

EASY JOINT TM

Pain Relief Spray

Spray Bottle

1f.l oz (30 mL)